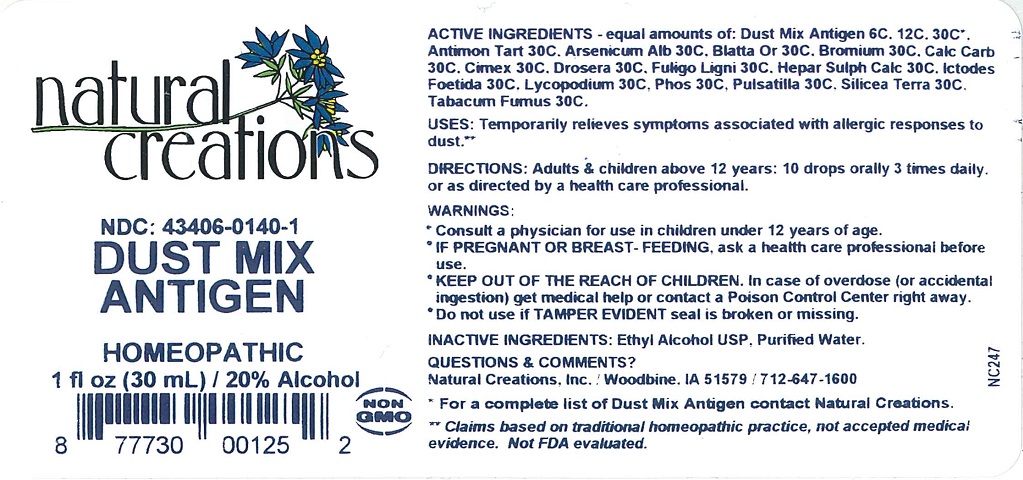 DRUG LABEL: Dust Mix Antigen
NDC: 43406-0140 | Form: LIQUID
Manufacturer: Natural Creations, Inc
Category: homeopathic | Type: HUMAN OTC DRUG LABEL
Date: 20181221

ACTIVE INGREDIENTS: ANTIMONY POTASSIUM TARTRATE 30 [hp_C]/1 mL; ARSENIC TRIOXIDE 30 [hp_C]/1 mL; BLATTA ORIENTALIS 30 [hp_C]/1 mL; BROMINE 30 [hp_C]/1 mL; OYSTER SHELL CALCIUM CARBONATE, CRUDE 30 [hp_C]/1 mL; CIMEX LECTULARIUS 30 [hp_C]/1 mL; DROSERA ROTUNDIFOLIA 30 [hp_C]/1 mL; CALCIUM SULFIDE 30 [hp_C]/1 mL; SYMPLOCARPUS FOETIDUS ROOT 30 [hp_C]/1 mL; LYCOPODIUM CLAVATUM SPORE 30 [hp_C]/1 mL; PHOSPHORUS 30 [hp_C]/1 mL; PULSATILLA VULGARIS 30 [hp_C]/1 mL; SILICON DIOXIDE 30 [hp_C]/1 mL; TOBACCO SMOKE 30 [hp_C]/1 mL
INACTIVE INGREDIENTS: WATER; ALCOHOL

Dust Mix Antigen

ACTIVE INGREDIENT

ACTIVE INGREDIENTS - equal amounts of: Dust Mix Antigen 6C, 12C, 30C, Antimon Tart 30C, Arsenicum Alb 30C, Blatta Or 30C, Bromium 30C, Calc Carb 30C, Cimex 30C, Drosera 30C, Hepar Sulph Calc 30C, Ictodes Foetida 30C, Lycopodium 30C, Phos 30C, Pulsatilla 30C, Silicea Terra 30C, Tabacum Fumus 30C

INDICATIONS AND USAGE

USES: Temporarily relieves symptoms associated with allergic responses to dust.**

PURPOSE

USES: Temporarily relieves symptoms associated with allergic responses to dust.**

DOSAGE AND ADMINISTRATION

DIRECTIONS: Adults & children above 12 years: 10 drops orally or as directed by a health care professional.

KEEP OUT OF REACH OF CHILDREN

KEEP OUT OF THE REACH OF CHILDREN. In case of overdose (or accidental ingestion) get medical help or contact a Poison Control Center right away.

WARNINGS:

- Consult a physician for use in children under 12 years of age.
- IF PREGNANT OR BREAST-FEEDING, ask a health care professional before use.
- KEEP OUT OF THE REACH OF CHILDREN. In case of overdose (or accidental ingestion) get medical help or contact a Poison Control Center right away.
- Do not use if TAMPER EVIDENT seal is broken or missing.

INACTIVE INGREDIENTS: Purified Water, Ethyl Alcohol USP

QUESTIONS & COMMENTS?

Natural Creations, Inc. / Woodbine, IA 51579 / 712-647-1600

REFERENCES

**Claims based on traditional homeopathic practice, not accepted medical evidence. Not FDA evaluated.

PACKAGE LABEL

NDC:43406-0140-1

Dust Mix Antigen

HOMEOPATHIC

1 fl oz (30mL) / 20% Alcohol